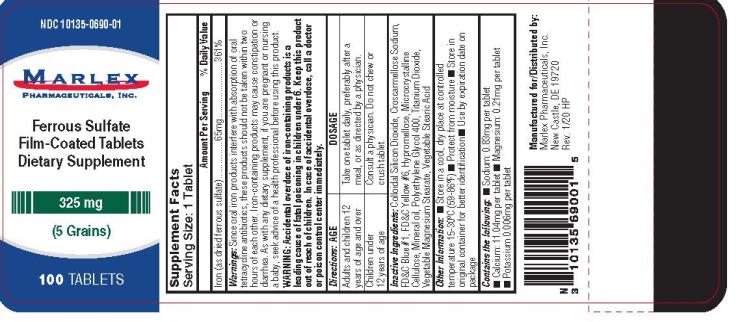 DRUG LABEL: Ferrous Sulfate
NDC: 10135-690 | Form: TABLET, FILM COATED
Manufacturer: Marlex Pharmaceuticals Inc
Category: other | Type: DIETARY SUPPLEMENT
Date: 20200320

ACTIVE INGREDIENTS: FERROUS SULFATE 65 mg/1 1
INACTIVE INGREDIENTS: HYPROMELLOSE, UNSPECIFIED; CROSCARMELLOSE SODIUM; CELLULOSE, MICROCRYSTALLINE; SILICON DIOXIDE; STEARIC ACID; MAGNESIUM STEARATE; FD&C BLUE NO. 1; FD&C YELLOW NO. 6; MINERAL OIL; POLYETHYLENE GLYCOL 400; TITANIUM DIOXIDE

ferrous sulfate 325mg tablets

Supplement Facts

Serving Size: 1 Tablet

Amount per Tablet % Daily Value

Iron (as dried ferrous sulfate) 65mg 361%

Active Ingredient (in each tablet) Purpose

Ferrous Sulfate Dietary Supplement

Warning:

Since oral iron products interfere with absorption of oral tetracycline antibiotics, these products should not be taken within two hours of each other. Iron-containing products may cause constipation or diarrhea. As with any dietary supplement, if you are pregnant or nursing a baby, seek advice of a health professional before using this product.

Warning: Accidental overdose of iron-containing products is a leading cause of fatal poisoning in children under 6. Keep this product out of reach of children. In case of accidental overdose, call a doctor or poison control center immediately.

Directions

Adults and Children 12 years of age and over:

1 tablet daily, preferably after a meal, or as directed by a physician.

Children under 12 years of age:

Consult a physician. Do not chew or crush tablet.

Inactive Ingredients:

Colloidal Silicon Dioxide, Croscarmellose Sodium, FD&C Blue #1, FD& C Yellow # 6, Hypromellose, Microcrystalline Cellulose, Mineral Oil, Polyethylene Glycol 400, Titanium Dioxide, Vegetable Magnesium Stearate, Vegetable Stearic Acid

Other Information:

- Store in a cool, dry place at controlled room temperature 15-30ºC (59-86ºF)
- Protect from moisture
- Store in original container for better identification
- Use by expiration date on package

Contains the following:

- Sodium: 0.83mg per tablet
- Calcium: 11.04mg per tablet
- Magnesium: 0.21mg per tablet
- Potassium: 0.006mg per tablet

Manufactured for/Distributed by:

Marlex Pharmaceuticals, Inc.,
New Castle, DE 19720

Rev. 1/20 HP

PRINCIPAL DISPLAY PANEL

NDC 10135-0690-01
Ferrous Sulfate
Film-Coated Tablets
325 mg
100 Tablets